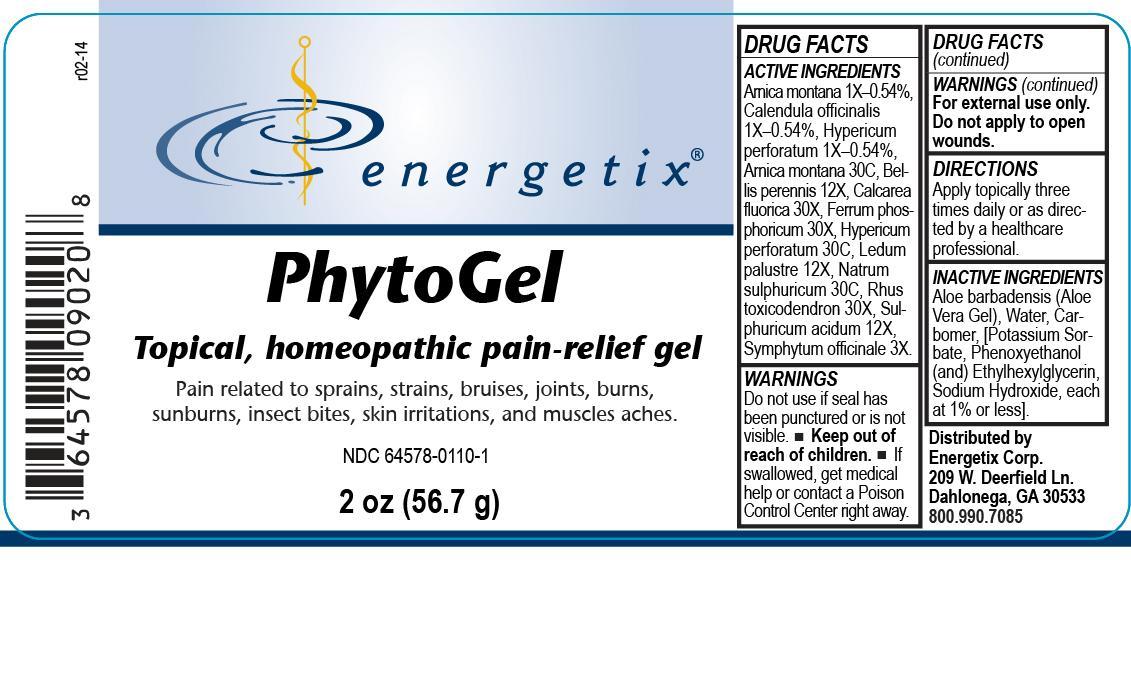 DRUG LABEL: PhytoGel
NDC: 64578-0110 | Form: GEL
Manufacturer: Energetix Corp
Category: homeopathic | Type: HUMAN OTC DRUG LABEL
Date: 20140225

ACTIVE INGREDIENTS: ARNICA MONTANA 1 [hp_X]/59.1 mL; BELLIS PERENNIS 12 [hp_X]/59.1 mL; CALCIUM FLUORIDE 30 [hp_X]/59.1 mL; CALENDULA OFFICINALIS FLOWERING TOP 1 [hp_X]/59.1 mL; FERRUM PHOSPHORICUM 30 [hp_X]/59.1 mL; HYPERICUM PERFORATUM 1 [hp_X]/59.1 mL; LEDUM PALUSTRE TWIG 12 [hp_X]/59.1 mL; SODIUM SULFATE 30 [hp_C]/59.1 mL; TOXICODENDRON PUBESCENS LEAF 30 [hp_X]/59.1 mL; SULFURIC ACID 12 [hp_X]/59.1 mL; COMFREY ROOT 3 [hp_X]/59.1 mL
INACTIVE INGREDIENTS: WATER 7.395801 mL/59.1 mL; ALCOHOL 1.84895 mL/59.1 mL; ALOE 46.494 g/59.1 mL

PhytoGel

Active Ingredients

Arnica montana 1X–0.54%, Calendula officinalis 1X–0.54%, Hypericum perforatum 1X–0.54%, Arnica montana 30C, Bellis perennis 12X, Calcarea fluorica 30X, Ferrum phosphoricum 30X, Hypericum perforatum 30C, Ledum palustre 12X, Natrum sulphuricum 30C, Rhus toxicodendron 30X, Sulphuricum acidum 12X, Symphytum officinale 3X

Warnings Section

If swallowed, get medical help or contact a Poison Control Center right away. For external use only. Do not apply to open wounds.

Do not use if seal has been punctured or is not visible.

Keep out of reach of children.

QUESTIONS

Distributed by Energetix Corp.

209 W. Deerfield Ln.

Dahlonega, GA 30533

800.990.7085

PURPOSE

Topical, homeopathic pain-relief gel.

INACTIVE INGREDIENT

Aloe barbadensis (Aloe Vera Gel), Water, Carbomer, [Potassium Sorbate, Phenoxyethanol (and) Ethylhexylglycerin, Sodium Hydroxide, each at 1% or less].

DOSAGE AND ADMINISTRATION

Apply topically three times daily or as directed by a healthcare professional.

INDICATIONS AND USAGE

Pain related to sprains, strains, bruises, joints, burns, sunburns, insect bites, skin irritations, and muscles aches.